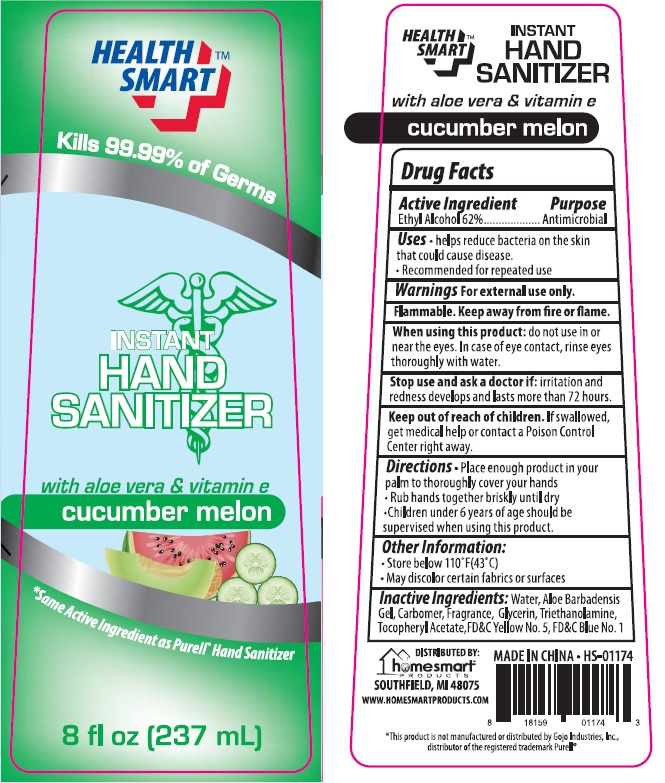 DRUG LABEL: Health Smart Instant Hand Sanitizer with aloe vera and vitamin e cucumber melon

NDC: 52862-401 | Form: SOLUTION
Manufacturer: International Wholesale, Inc.
Category: otc | Type: HUMAN OTC DRUG LABEL
Date: 20141120

ACTIVE INGREDIENTS: ALCOHOL 62 mL/100 mL
INACTIVE INGREDIENTS: WATER; ALOE VERA LEAF; CARBOMER HOMOPOLYMER TYPE C (ALLYL PENTAERYTHRITOL CROSSLINKED); GLYCERIN; TROLAMINE; .ALPHA.-TOCOPHEROL ACETATE; FD&C YELLOW NO. 5; FD&C BLUE NO. 1

Instant Hand Sanitizer

Drug Facts

Active Ingredients

Ethyl Alcohol 62%

Purpose

Antimicrobial

Uses

- helps reduce bacteria on the skin that could cause disease
- Recommended for repeated use

Warnings

For external use only.

Flammable. Keep away from fire or flame.

When using this product do not use in or near the eyes. In case of eye contact, rinse eyes thoroughly with water.

Stop use and ask a doctor if: irritation and redness develops and lasts more than 72 hours.

Keep out of reach of children. If swallowed, get medical help or contact a Poison Control Center right away.

Directions

- Place enough product in your palm to thoroughly cover your hands
- Rub hands together briskly until dry
- Children under 6 years of age should be supervised when using this product.

Other information

- Store below 110°F (43°C)
- May discolor certain fabrics or surfaces.

Inactive ingredients

Water, Aloe Barbadensis Gel, Carbomer, Glycerin, Triethanolamine, Tocopheryl Acetate, FD&C Yellow No. 5, FD&C Blue No.1

MADE IN CHINA.

DISTRIBUTED BY:
homesmartTM
PRODUCTS
SOUTHFIELD, MI 48075
WWW.HOMESMARTPRODUCTS.COM

* This product is not manufactured or distributed by Gojo Industries, Inc. distributor of the registered trademark Purell®

Package Label

HEALTH SMARTTM
Kills 99.99% of Germs
INSTANT
HAND
SANITIZER
with aloe vera & vitamin e
cucumber melon
*Same Active ingredient as Purell® Hand Sanitizer
8 fl oz [237 mL]